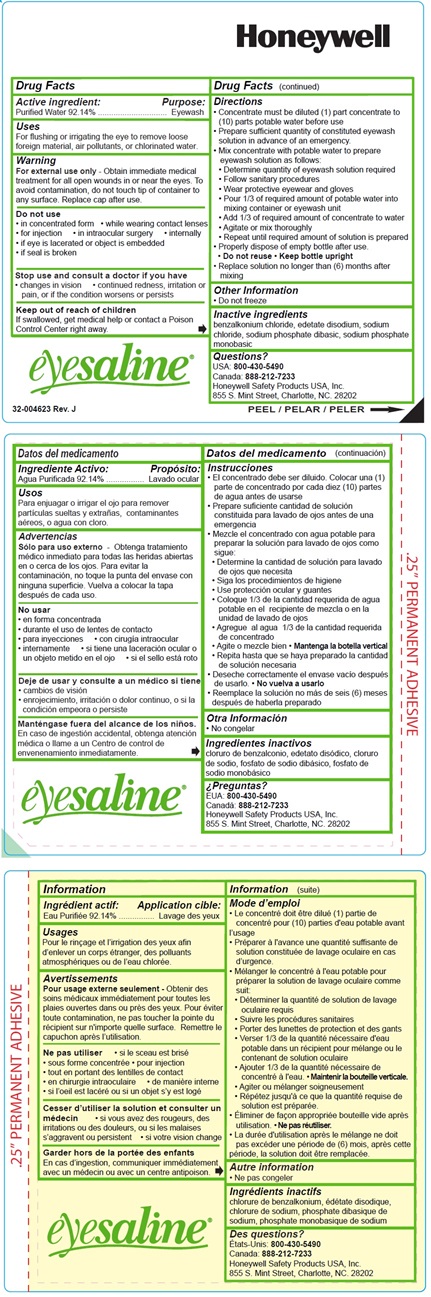 DRUG LABEL: Eyesaline Eyewash Concentrate
NDC: 0498-2501 | Form: LIQUID
Manufacturer: Honeywell Safety Products, Inc.
Category: otc | Type: HUMAN OTC DRUG LABEL
Date: 20250207

ACTIVE INGREDIENTS: WATER 92.14 L/100 L
INACTIVE INGREDIENTS: SODIUM PHOSPHATE, MONOBASIC, MONOHYDRATE; SODIUM PHOSPHATE, DIBASIC, ANHYDROUS; SODIUM CHLORIDE; EDETATE DISODIUM; BENZALKONIUM CHLORIDE

32-000509-0000-HS (0498-2501-01), and 32-000513-0000-H5 (0498-2501-01) Concentrate Products

ACTIVE INGREDIENT

Purified Water 92.14%

PURPOSE

Eyewash

INDICATIONS AND USAGE

For flushing the eye to remove loose foreign material, air pollutants or chlorinated water

WARNINGS

For external use only- Obtain immediate medical treatment for all open wounds in or near eyes. To avoid contamination, do not touch tip of container to any surface. Replace cap after use.

DO NOT USE

In concentrated form

While wearing contact lenses

For injection

In intraocular sugery

Internaly

if eye is lacerated or object is imbeded

if seal is broken

STOP USE

Changes in vision, continued redness, irritation or pain, or if the condition worsens or persist

KEEP OUT OF REACH OF CHILDREN

If swallowed, get medical help or contact a Poison Control Center right away.

Directions

Concentrate must be diluted (1) part concentrate to (10) parts potable water before use
• Prepare sufficient quantity of constituted eyewash solution in advance of an emergency.
• Mix concentrate with potable water to prepare eyewash solution as follows:
• Determine quantity of eyewash solution required
• Follow sanitary procedures
• Wear protective eyewear and gloves
• Pour 1/3 of required amount of potable water into mixing container or eyewash unit
• Add 1/3 of required amount of concentrate to water
• Agitate or mix thoroughly
• Repeat until required amount of solution is prepared
• Properly dispose of empty bottle after use.
• Do not reuse • Keep bottle upright
• Replace solution no longer than (6) months after mixing

INACTIVE INGREDIENT

Benzalkonium chloride, edetate disodium, sodium chloride, sodium phosphate dibasic, sodium phosphate monobasic

QUESTIONS

USA: 800 430-5490

Canada: 888 212-7233
Honeywell Safety Products USA, 855 S. Mint Street, Charlotte, NC 28202